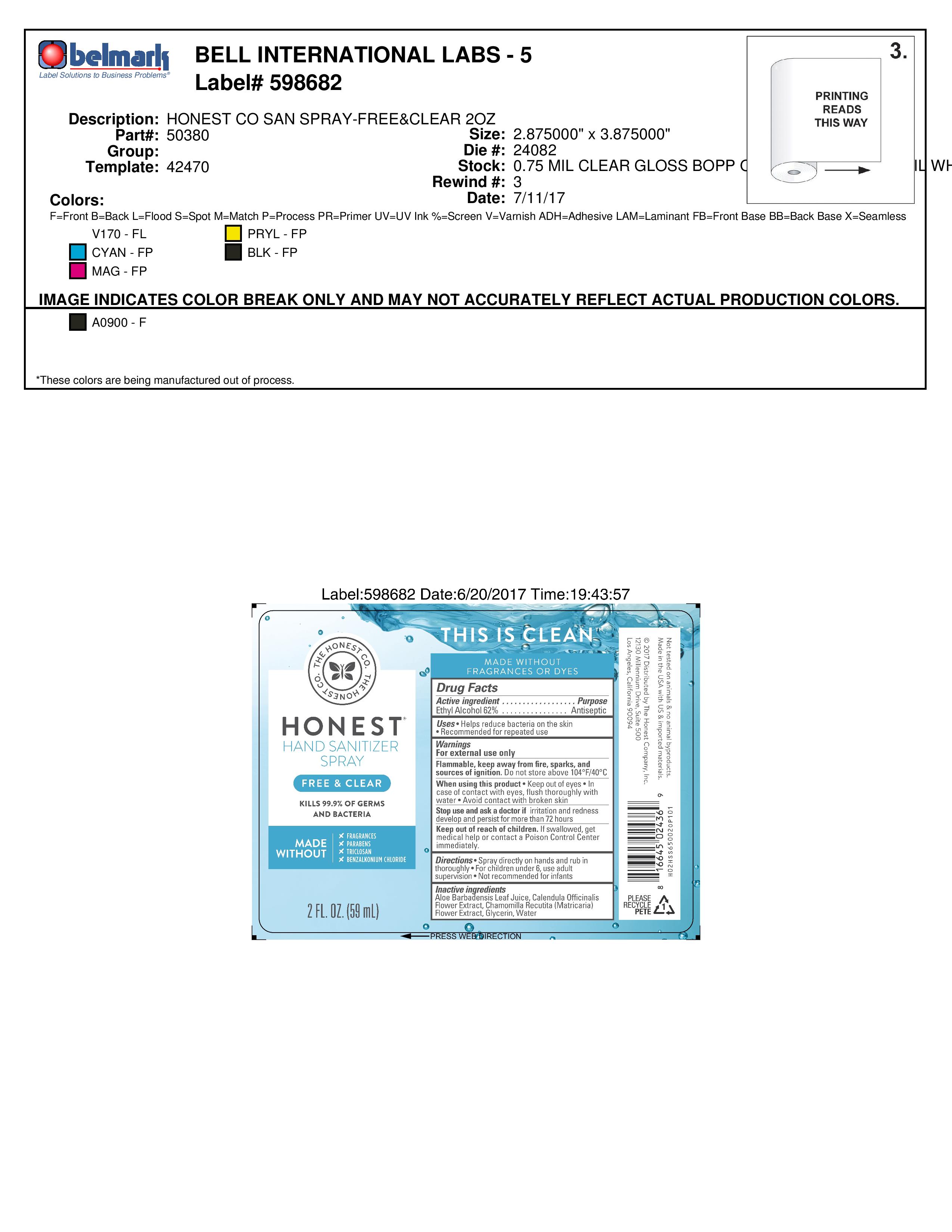 DRUG LABEL: Hand Sanitizer
NDC: 69366-311 | Form: SPRAY
Manufacturer: The Honest Company
Category: otc | Type: HUMAN OTC DRUG LABEL
Date: 20241219

ACTIVE INGREDIENTS: ALCOHOL 62 mL/100 mL
INACTIVE INGREDIENTS: WATER; CHAMOMILE; CALENDULA OFFICINALIS FLOWER; GLYCERIN; ALOE VERA LEAF

Honest Company Hand Sanitizer Spray Free & Clear 2 oz

Active ingredient

Ethyl Alcohol 62%

Purpose

Antiseptic

Uses

Helps reduce bacteria on the skin

Recommended for repeated use

Warnings

For external use only

Flammable, keep away from fire, sparks, and sources of ignition. Do not store above 104oF/40oC

When using this product, keep out of eyes. In case of contact with eyes, flush thoroughly with water. Avoid contact with broken skin.

Stop use and ask a doctor if irritation and redness develop and persist for more than 72 hours

Keep out of reach of children. If swallowed, get medcal help or contact a Poison Control Center immediately

Directions

Spray directly on hands and rub in thoroughly. For children under 6, use adult supervision. Not recommended for infants

Inactive ingredients

Aloe Barbadensis Leaf Juice, Claendula Officinalis Flower Extract, Chamomilla Recutita (Matricaria) Flower Extract, Glycerin, Water